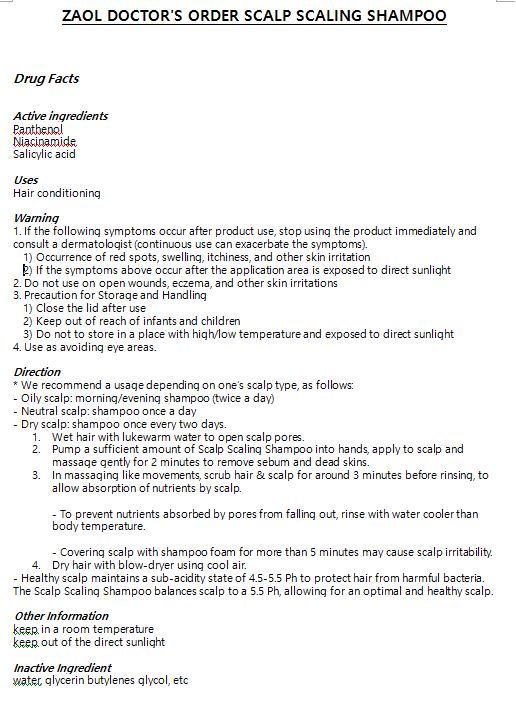 DRUG LABEL: ZAOL DOCTORS ORDER SCALP SCALING
NDC: 71175-0003 | Form: SHAMPOO
Manufacturer: zaol
Category: otc | Type: HUMAN OTC DRUG LABEL
Date: 20180607

ACTIVE INGREDIENTS: NIACINAMIDE 0.1 g/100 mL; PANTHENOL 0.2 g/100 mL; SALICYLIC ACID 0.2 g/100 mL
INACTIVE INGREDIENTS: BUTYLENE GLYCOL; WATER

ACTIVE INGREDIENT

Panthenol, Niacinamide, salicylic acid

INACTIVE INGREDIENT

Water, Glycerin, Butylene Glycol, etc.

PURPOSE

Hair conditioning

Keep out of reach of the children

WARNINGS

1. If the following symptoms occur after product use, stop using the product immediately and consult a dermatologist (continuous use can exacerbate the symptoms).
1) Occurrence of red spots, swelling, itchiness, and other skin irritation
2) If the symptoms above occur after the application area is exposed to direct sunlight

2. Do not use on open wounds, eczema, and other skin irritations

3. Precaution for Storage and Handling
1) Close the lid after use
2) Keep out of reach of infants and children
3) Do not to store in a place with high/low temperature and exposed to direct sunlight

4. Use as avoiding eye areas.

INDICATIONS AND USAGE

* We recommend a usage depending on one’s scalp type, as follows:

- Oily scalp: morning/evening shampoo (twice a day)

- Neutral scalp: shampoo once a day

- Dry scalp: shampoo once every two days.

1. Wet hair with lukewarm water to open scalp pores.
2. Pump a sufficient amount of Scalp Scaling Shampoo into hands, apply to scalp and massage gently for 2 minutes to remove sebum and dead skins.
3. In massaging like movements, scrub hair & scalp for around 3 minutes before rinsing, to allow absorption of nutrients by scalp.
  - To prevent nutrients absorbed by pores from falling out, rinse with water cooler than body temperature.
  - Covering scalp with shampoo foam for more than 5 minutes may cause scalp irritability.
4. Dry hair with blow-dryer using cool air.

- Healthy scalp maintains a sub-acidity state of 4.5-5.5 Ph to protect hair from harmful bacteria. The Scalp Scaling Shampoo balances scalp to a 5.5 Ph, allowing for an optimal and healthy scalp.

DOSAGE AND ADMINISTRATION

For external use only